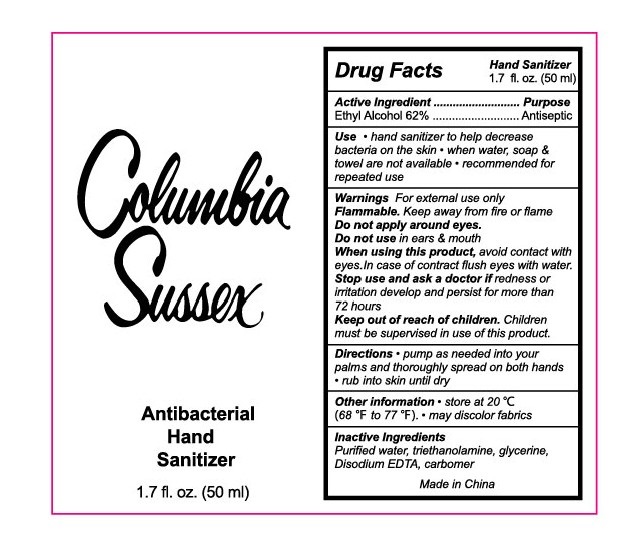 DRUG LABEL: Antibacterial Hand Sanitizer
NDC: 71734-319 | Form: LIQUID
Manufacturer: JIANGMEN SHUIZIRUN SANITARY ARTICLES CO., LTD.
Category: otc | Type: HUMAN OTC DRUG LABEL
Date: 20200704

ACTIVE INGREDIENTS: ALCOHOL 62 mL/100 mL
INACTIVE INGREDIENTS: WATER; GLYCERIN; TROLAMINe; EDETATE DISODIUM

Active ingredient

Ethyl Alcohol ...... 62%

Purpose

Antiseptic

Use

- Hand sanitizer to help decrease bacterin on the skin.
- When water, soap and towel are not available
- Recommended for repeated use.

Warnings

For external use only.

Flammable, keep away from fire or flame

Do not use in ears and mouth

When using this product, avoid contact with eyes. In case of contact flush eyes with water.

Stop use and ask a doctor if redness or irritation develop and persist for more than 72 hours

Keep out of reach of children.

Children must be supervised in use of this product.

Directions

- Pump as needed into your palms and thoroughly spread on both hands.
- Rub into skin until dry.

Inactive ingredients

Purified Water, Glycerin, Carbomer, Triethanolamine, Disodium EDTA

Other Information

- Store at 20 ℃ (68 to 77 ℉)
- May discolor fabrics.